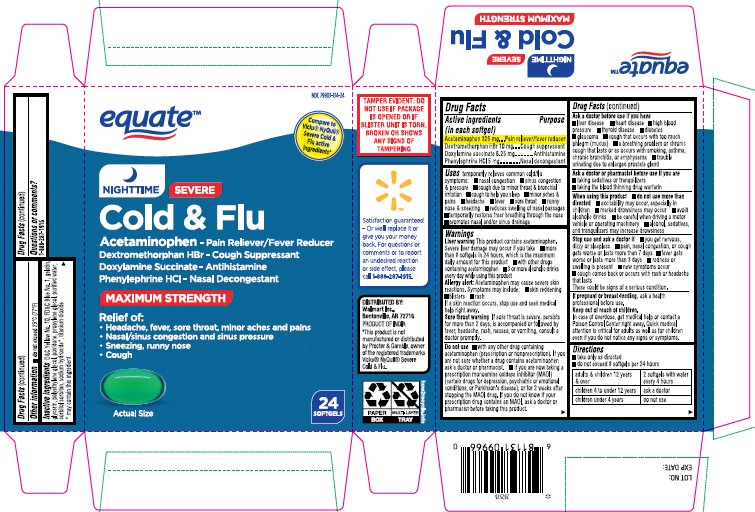 DRUG LABEL: NIGHTTIME SEVERE COLD AND FLU
NDC: 79903-134 | Form: CAPSULE, LIQUID FILLED
Manufacturer: Wal-Mart Stores Inc
Category: otc | Type: HUMAN OTC DRUG LABEL
Date: 20260126

ACTIVE INGREDIENTS: ACETAMINOPHEN 325 mg/1 1; DEXTROMETHORPHAN HYDROBROMIDE 10 mg/1 1; DOXYLAMINE SUCCINATE 6.25 mg/1 1; PHENYLEPHRINE HYDROCHLORIDE 5 mg/1 1
INACTIVE INGREDIENTS: D&C YELLOW NO. 10; FD&C BLUE NO. 1; GELATIN; GLYCERIN; POLYETHYLENE GLYCOL 400; POVIDONE K30; PROPYLENE GLYCOL; SODIUM HYDROXIDE; SORBITOL; TITANIUM DIOXIDE

NIGHTTIME SEVERE COLD AND FLU

Active ingredients (in each softgel)

Acetaminophen 325 mg

Dextromethorphan hydrobromide 10 mg

Doxylamine succinate 6.25 mg

Phenylephrine hydrochloride 5 mg

Purpose

Pain reliever/fever reducer

Cough suppressant

Antihistamine

Nasal decongestant

Uses

temporarily relieves common cold/flu symptoms:

- nasal congestion
- sinus congestion & pressure
- cough due to minor throat & bronchial irritation
- cough to help you sleep
- minor aches & pains
- headache
- fever
- sore throat
- runny nose & sneezing
- reduces swelling of nasal passages
- temporarily restores freer breathing through the nose
- promotes nasal and/or sinus drainage

Warnings

Liver warning This product contains acetaminophen.
Severe liver damage may occur if you take
• more than 8 softgels in 24 hours, which is the maximum daily amount for this product
• with other drugs containing acetaminophen
• 3 or more alcoholic drinks every day while using this product
Allergy alert: Acetaminophen may cause severe skin reactions. Symptoms may include:
• skin reddening
• blisters
• rash
If a skin reaction occurs, stop use and seek medical help right away.
Sore throat warning If sore throat is severe, persists for more than 2 days, is accompanied or followed by fever, headache, rash, nausea, or vomiting, consult a doctor promptly.

Do not use

• with any other drug containing acetaminophen (prescription or nonprescription). If you are not sure whether a drug contains acetaminophen ask a doctor or pharmacist.
• if you are now taking a prescription monoamine oxidase inhibitor (MAOI) (certain drugs for depression, psychiatric or emotional conditions, or Parkinson's disease), or for 2 weeks after stopping the MAOI drug. If you do not know if your prescription drug contains an MAOI, ask a doctor or pharmacist before taking this product.

Ask a doctor before use if you have
• liver disease
• heart disease
• high blood pressure
• thyroid disease
• diabetes
• glaucoma
• cough that occurs with too much phlegm (mucus)
• a breathing problem or chronic cough that lasts or as occurs with smoking, asthma, chronic bronchitis, or emphysema
• trouble urinating due to enlarged prostate gland

Ask a doctor or pharmacist before use if you are
• taking sedatives or tranquilizers
• taking the blood thinning drug warfarin

When using this product
• do not use more than directed
• excitability may occur, especially in children
• marked drowsiness may occur n avoid alcoholic drinks
• be careful when driving a motor vehicle or operating machinery
• alcohol, sedatives, and tranquilizers may increase drowsiness

Stop use and ask a doctor if
• you get nervous, dizzy or sleepless
• pain, nasal congestion, or cough gets worse or lasts more than 7 days n fever gets worse or lasts more than 3 days n redness or swelling is present
• new symptoms occur
• cough comes back or occurs with rash or headache that lasts
These could be signs of a serious condition.

PREGNANCY OR BREAST FEEDING

If pregnant or breast-feeding, ask a health professional before use.

Keep out of reach of children. In case of overdose, get medical help or contact a Poison Control Center right away. Quick medical attention is critical for adults as well as for children even if you do not notice any signs or symptoms.

Directions

- take only as directed
- ndo not exceed 8 softgels per 24 hour

adults & children 12 years & over | 2 softgels with water every 4 hours
children 4 to under 12 years | ask a doctor
children under 4 years | do not use

Other information

• do not exceed 25°C (77°F)

Inactive Ingredients

D&C Yellow No. 10, FD&C Blue No. 1, gelatin, glycerin, polyethylene glycol, povidone, propylene glycol, purified water, sorbitol sorbitan, sodium hydroxide*, titanium dioxide
* may contain this ingredient

Questions or comments?

1-888-333-9792

PACKAGE LABEL

Principal Display Panel

Carton